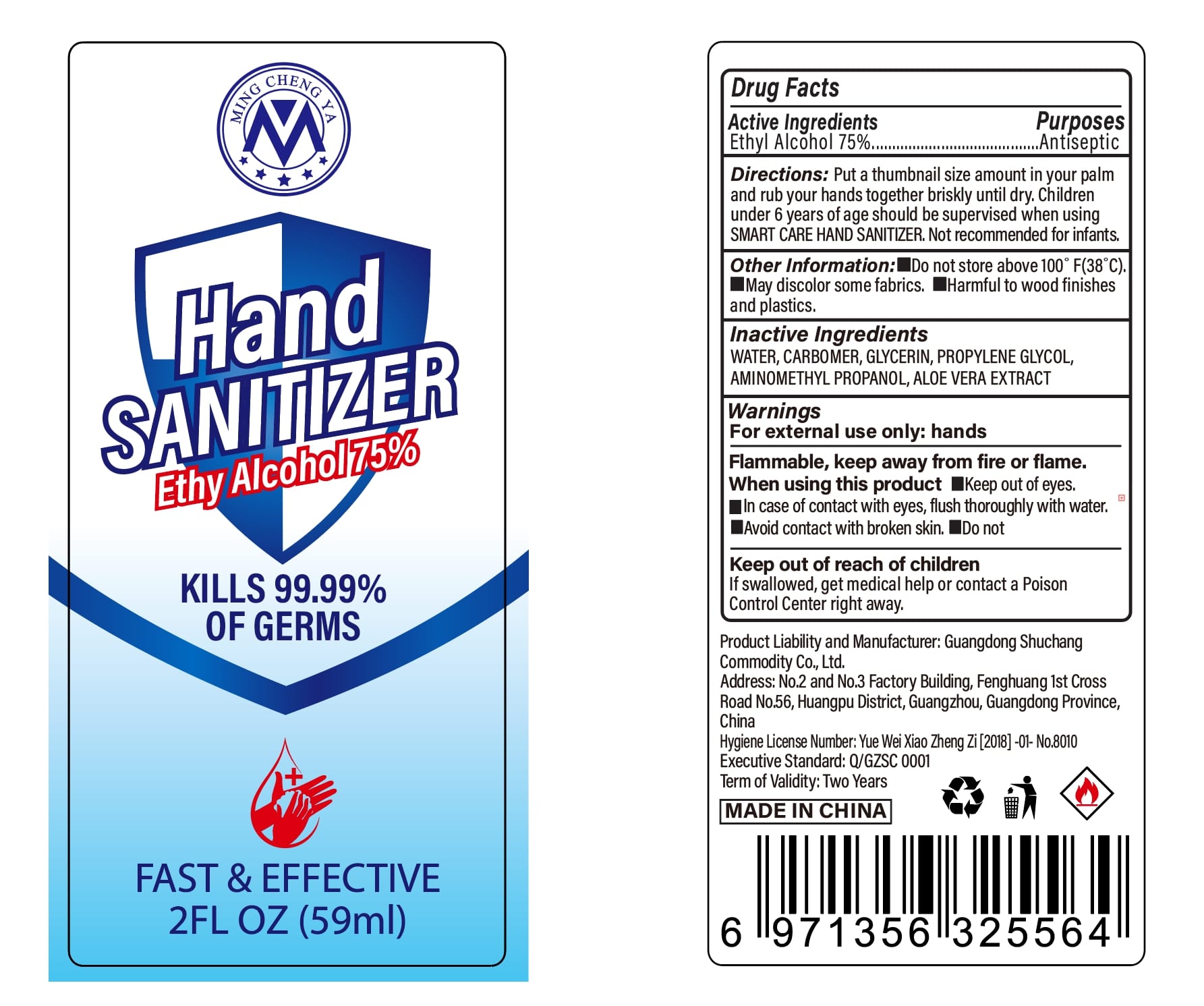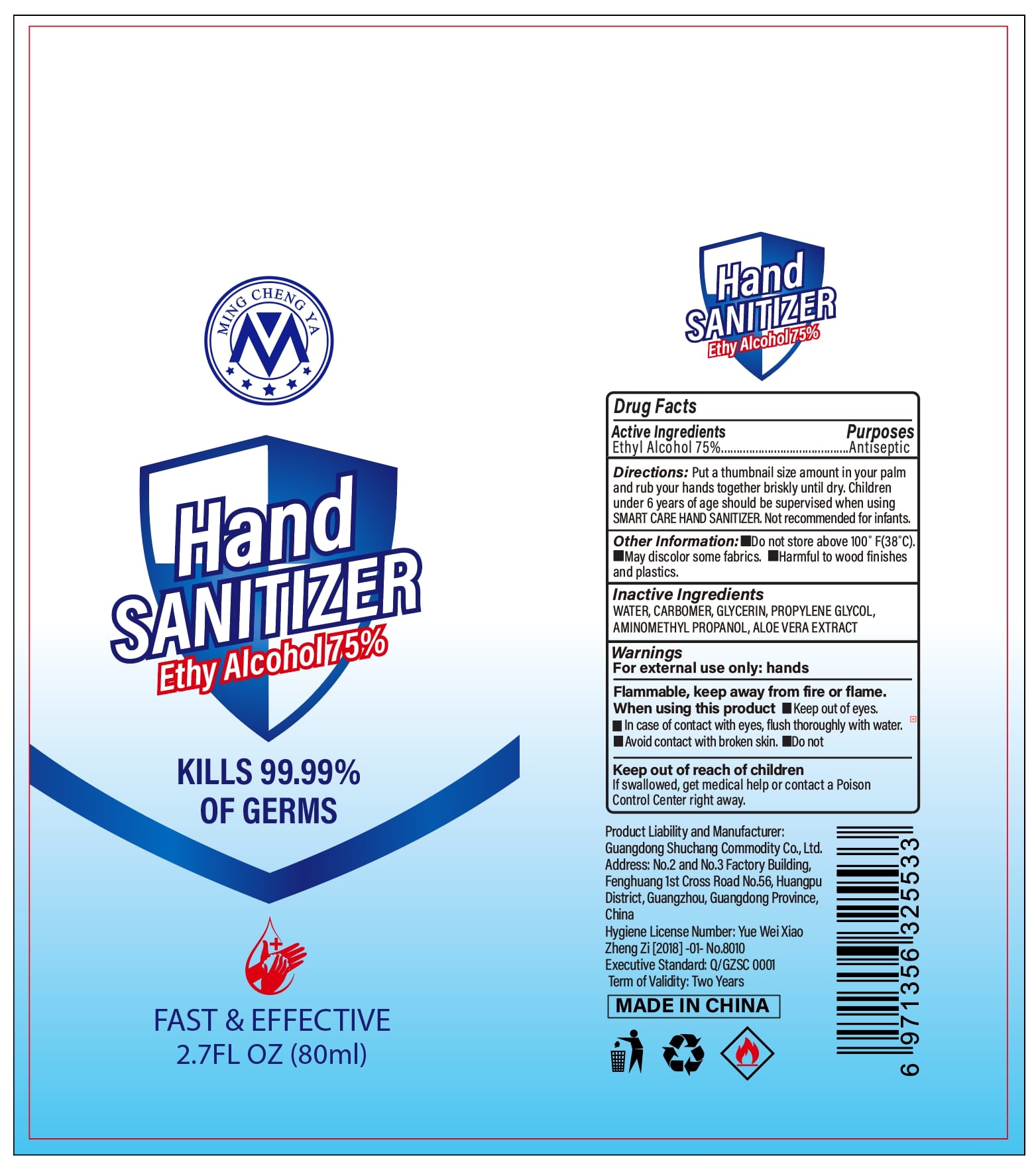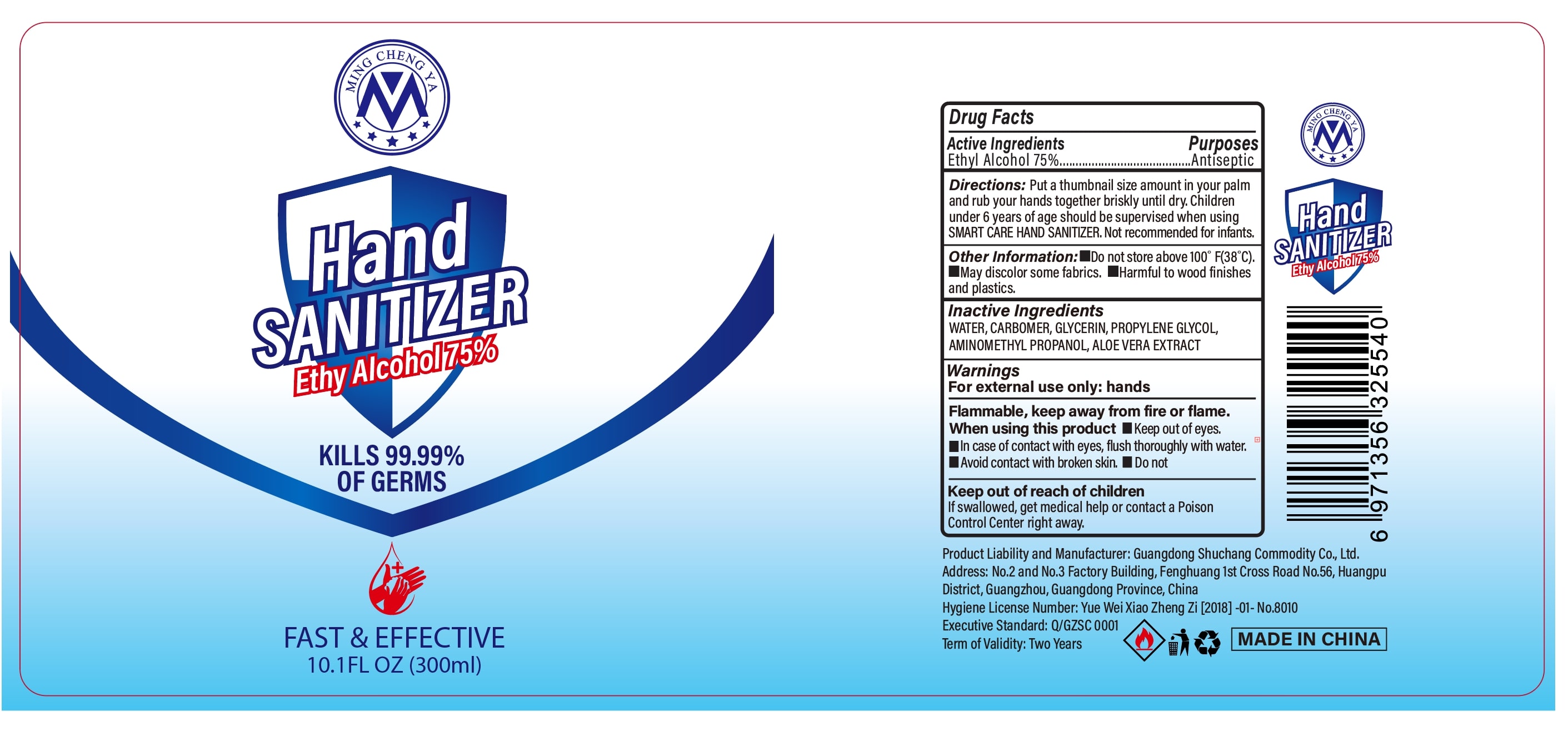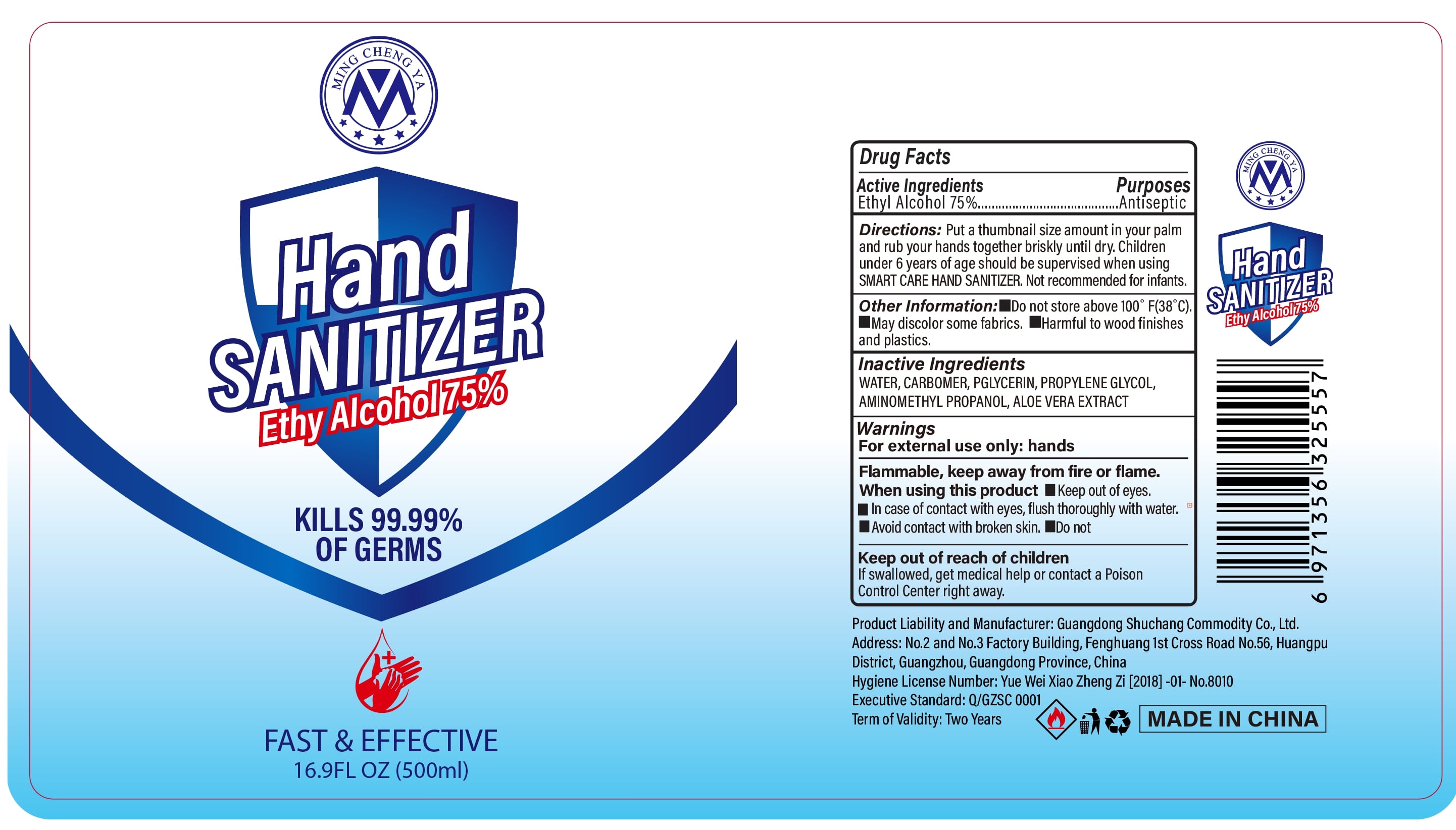 DRUG LABEL: HAND SANITIZER
NDC: 75442-001 | Form: GEL
Manufacturer: Guangdong Shuchang daily necessities Co., Ltd.
Category: otc | Type: HUMAN OTC DRUG LABEL
Date: 20200423

ACTIVE INGREDIENTS: ALCOHOL 75 mL/100 mL
INACTIVE INGREDIENTS: CARBOMER HOMOPOLYMER, UNSPECIFIED TYPE; PROPYLENE GLYCOL; ALOE VERA LEAF; WATER; GLYCERIN; AMINOMETHYLPROPANOL

Hand SANITIZER

Active Ingredients

Ethyl Alcohol 75%

Purposes

Antiseptic

Warnings

For external use only:hands

Flammable, keep away from fire or flame.

When using this product

Keep out of eyes.In case of contact with eyes,flush thoroughly with water.

Avoid contact with broken skin.Do not

Keep out of reach of children

If swallowed,get medical help or contact a Poison Control Center right away.

Directions

Put a thumbnail size amount in your palm and rub your hands together briskly until dry.Children under 6 years of age should be supervised when using SMART CARE HAND SANITIZER,Not recommended for infants.

Other Information

Do not store above 100°F(38℃).

May discolor some fabrics.

Harmful to wood finishes and plastics.

Inactive Ingredients

WATER, CARBOMER, GLYCERIN, PROPYLENE GLYCOL,AMINOMETHYL PROPANOL, ALOE VERA EXTRACT.